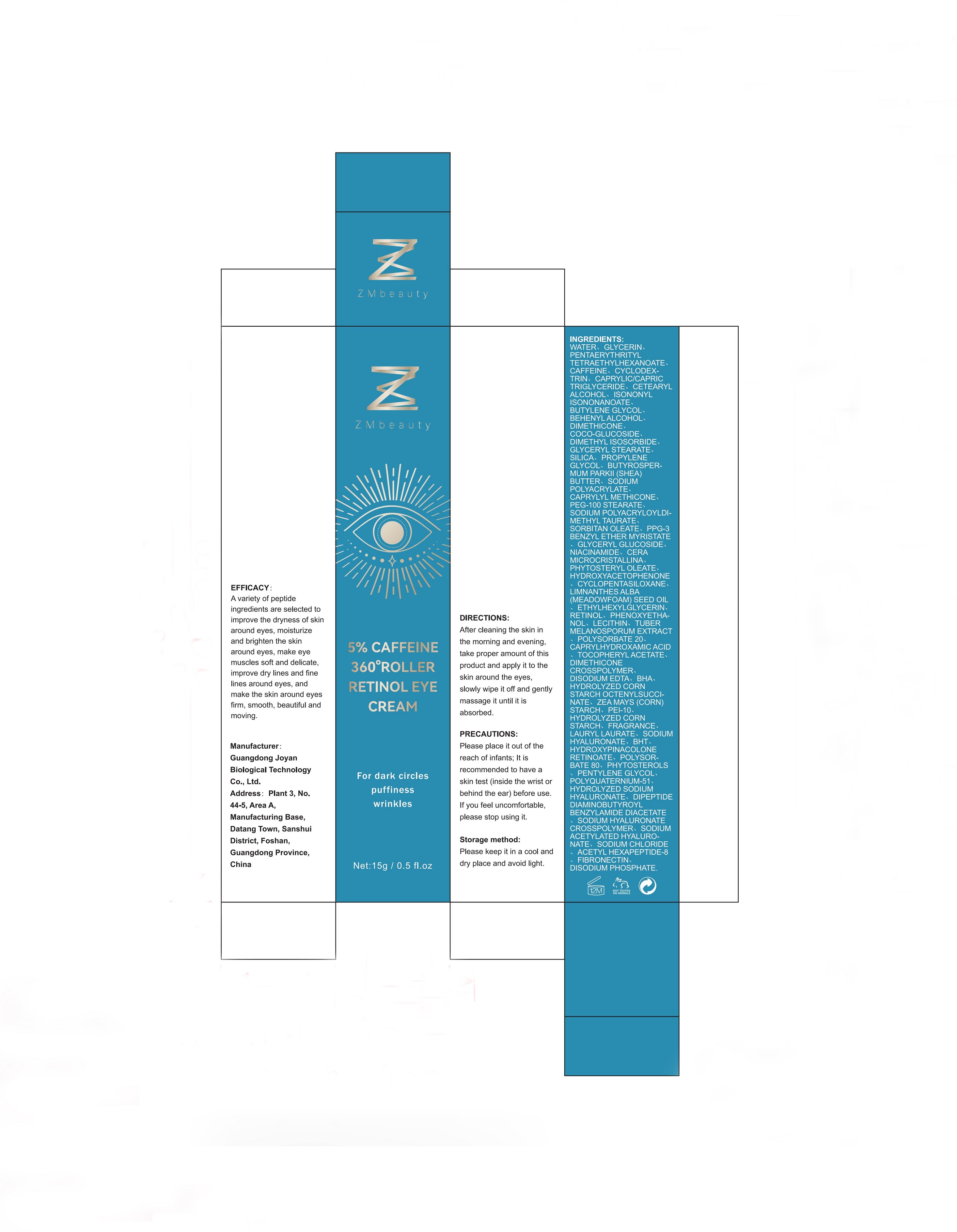 DRUG LABEL: Caffeine Cream
NDC: 84716-001 | Form: EMULSION
Manufacturer: Shenzhen Boyang E-commerce Co.
Category: otc | Type: HUMAN OTC DRUG LABEL
Date: 20240918

ACTIVE INGREDIENTS: CAFFEINE 75 mg/15 g; RETINOL 15 mg/15 g
INACTIVE INGREDIENTS: GLYCERIN 90 mg/15 g; WATER 747 mg/15 g

ACTIVE INGREDIENTS

CAFFEINE 5%
RETINOL 1%

PURPOSE

For dark circles puffiness wrinkles. A variety of peptide ingredients are selected to improve the dryness of skin around eyes, moisturize and brighten the skin around eyes, make eye muscles soft and delicate,improve dry lines and fine lines around eyes, and make the skin around eyes firm, smooth, beautiful and moving.

Uses

After cleaning the skin inthe morning and evening,take proper amount of thisproduct and apply it to the skin around the eyes,slowly wipe it off and gently massage it until it is absorbed.

Warnings

Please place it out of the reach of infants; lt is recommended to have a skin test (inside the wrist or behind the ear) before use.lf you feel uncomfortable,please stop using it.

Stop use and ask a doctor if

lt is recommended to have a skin test (inside the wrist orbehind the ear) before use.If you feel uncomfortable,please stop using it.

Do not use

on damaged or broken skin

Keep out of reach of children.

Please place it out of the reach of infants；If swallowed, get medical help or contact a Poison Control Center right away.

When using this product

keep out of eyes. Rinse with water to remove.

uses and storage method

After cleaning the skin in the morning and evening,take proper amount of this product and apply it to the skin around the eyes,slowly wipe it off and gently massage it until it is absorbed.Please keep it in a cool and dry place and avoid light.